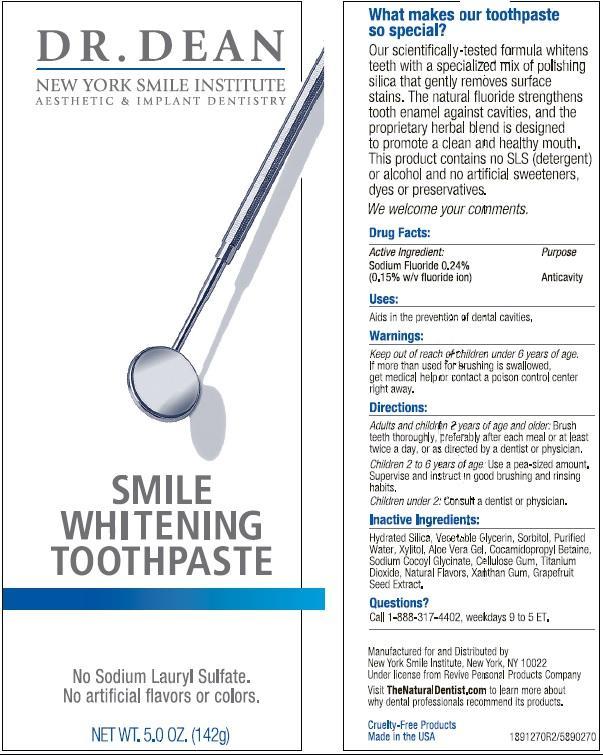 DRUG LABEL: The Natural Dentist
NDC: 34362-0270 | Form: PASTE, DENTIFRICE
Manufacturer: Caldwell Consumer Health LLC
Category: otc | Type: HUMAN OTC DRUG LABEL
Date: 20210125

ACTIVE INGREDIENTS: SODIUM FLUORIDE 0.2430 g/100 g
INACTIVE INGREDIENTS: WATER; SORBITOL; XYLITOL; ALOE VERA LEAF; TITANIUM DIOXIDE; GLYCERIN; HYDRATED SILICA; XANTHAN GUM; CITRUS PARADISI SEED; COCAMIDOPROPYL BETAINE; SODIUM COCOYL GLYCINATE; CARBOXYMETHYLCELLULOSE SODIUM

Drug Facts

Active ingredient

Sodium fluoride 0.24% w/w (0.15% w/v fluoride ion)...............Anticavity

Uses

aids in the prevention of dental cavities

Stop use and ask a dentist if the sensitivity persists or worsens. Sensitive teeth may indicate a serious problem that may need prompt care by a dentist.

Do not use if safety seal is broken.

Keep out of reach of children under 6 years of age. If more than used for brushing is accidentally swallowed, get medical help or contact a Poison Control Center right away.

Directions

Adults and children 2 years and older: Brush teeth thoroughly after meals, at least twice a day or as directed by a dentist. Do not swallow.

Children under 2 years of age: Consult a dentist or physician.

DOSAGE AND ADMINISTRATION

Children 2 to 6 years of age: Use a pea sized amount and supervise until good brushing habits are established. Children under 2 years of age: ask a dentist.

Other Information

Store tube standing up with cap tightly closed.

Inactive ingredients

Hydrated Silica, Glycerin, Sorbitol, Water, Xylitol, Cocamidopropyl Betaine, Sodium Cocoyl Glycinate, Aloe barbadensis Leaf Juice, Cellulose Gum, Citrus grandis (Grapefruit) Seed Extract, Titanium Dioxide, Xanthan Gum, Flavor.

PACKAGE LABEL

mm1.jpg